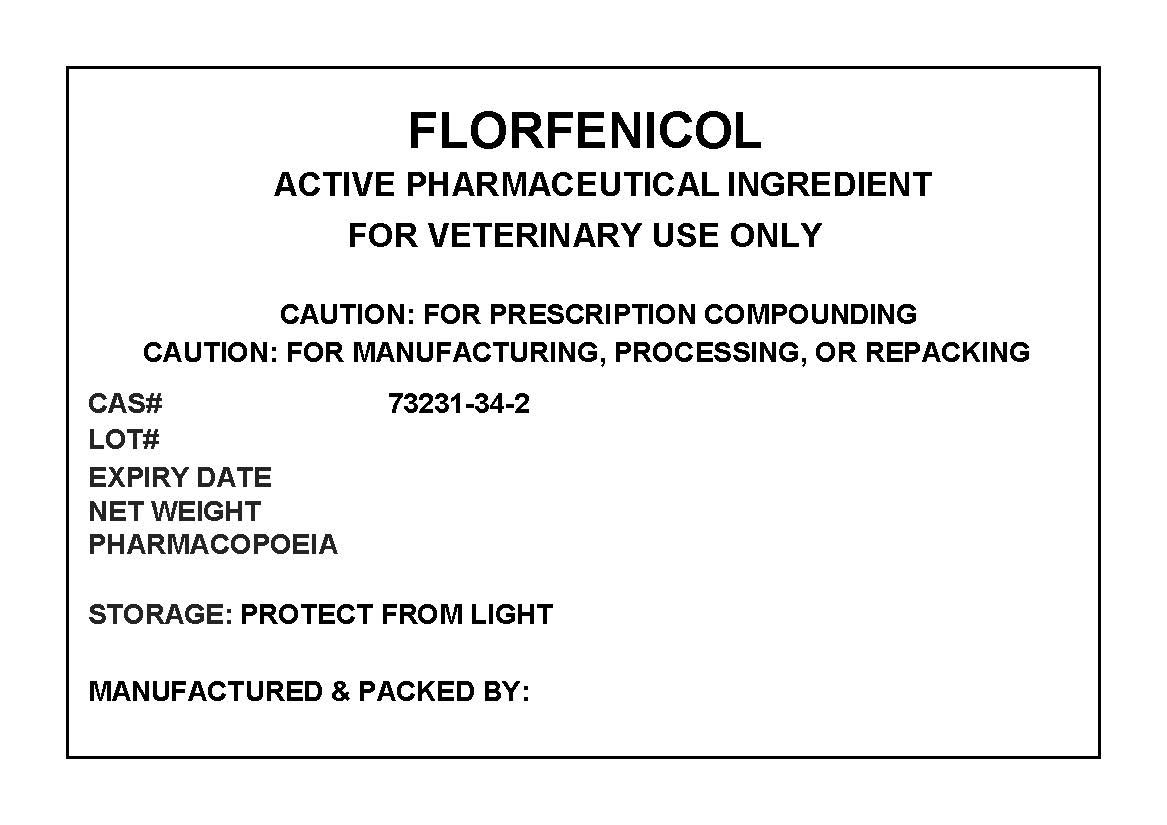 DRUG LABEL: FLORFENICOL
NDC: 72969-110 | Form: POWDER
Manufacturer: PROFESSIONAL GROUP OF PHARMACISTS NEW YORK LLC
Category: other | Type: BULK INGREDIENT
Date: 20210329

ACTIVE INGREDIENTS: FLORFENICOL 1 g/1 g

FLORFENICOL

PACKAGE LABEL

florfenicollabel.jpg